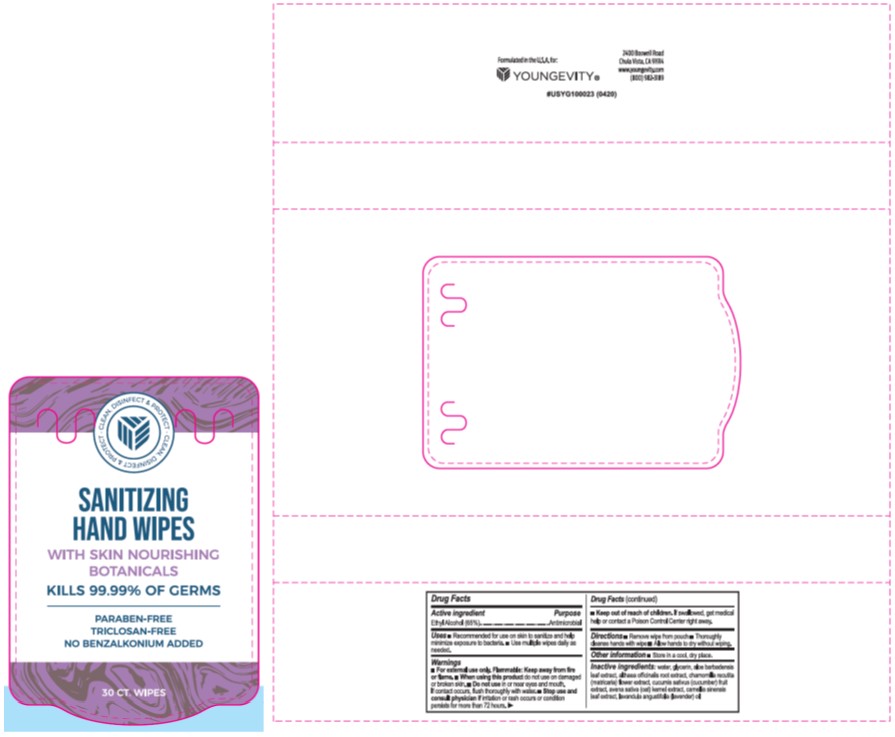 DRUG LABEL: Hand Sanitizer
NDC: 80986-100 | Form: CLOTH
Manufacturer: Youngevity International Inc.
Category: otc | Type: HUMAN OTC DRUG LABEL
Date: 20201118

ACTIVE INGREDIENTS: ALCOHOL 65 mL/100 mL
INACTIVE INGREDIENTS: GLYCERIN; LAVENDER OIL; WATER; ALOE VERA LEAF; CUCUMBER; ALTHAEA OFFICINALIS ROOT; OAT; GREEN TEA LEAF; CHAMOMILE

Youngevity International Inc.
SANITIZING HAND WIPES

Active Ingredient

Ethyl Alcohol (65%)

Purpose

Antimicrobial

Uses

• Recommended for use on skin to sanitize and help minimize exposure to bacteria.

• Use multiple wipes daily as needed.

Warnings

• For external use only. Flammable: Keep away from fire or flame. • When using this product do not use on damaged or broken skin. • Do not use in or near eyes and mouth.
If contact occurs, flush thoroughly with water. • Stop use and consult physician if irritation or rash occurs or condition persists for more than 72 hours.

Keep out of reach of children

If swallowed, get medical help or contact a Poison Control Center right away.

Directions

• Remove wipe from pouch

• Thoroughly cleanse hands with wipe

• Allow hands to dry without wiping

Other information

• Store in a cool, dry place.

Inactive ingredients

water, glycerin, aloe barbadensis leaf extract, althaea officinalis root extract, chamomilla recutita (matricaria) flower extract, cucumis sativus (cucumber) fruit extract, avena sativa (oat) kernel extract, camellia sinensis leaf extract, lavandula angustifolia (lavender) oil

Label

CLEAN. DISINFECT & PROTECT.

SANITIZING HAND WIPES

WITH SKIN NOURISHING BOTANICALS

KILLS 99.99% OF GERMS

PARABEN-FREE

TRICLOSAN-FREE

NO BENZALKONIUM ADDED

30 CT. WIPES

Formulated in the U.S.A. for:

YOUNGEVITY

2400 Boswell Road

Chula Vista, CA 91914

www.youngevity.com

(800) 982-3189